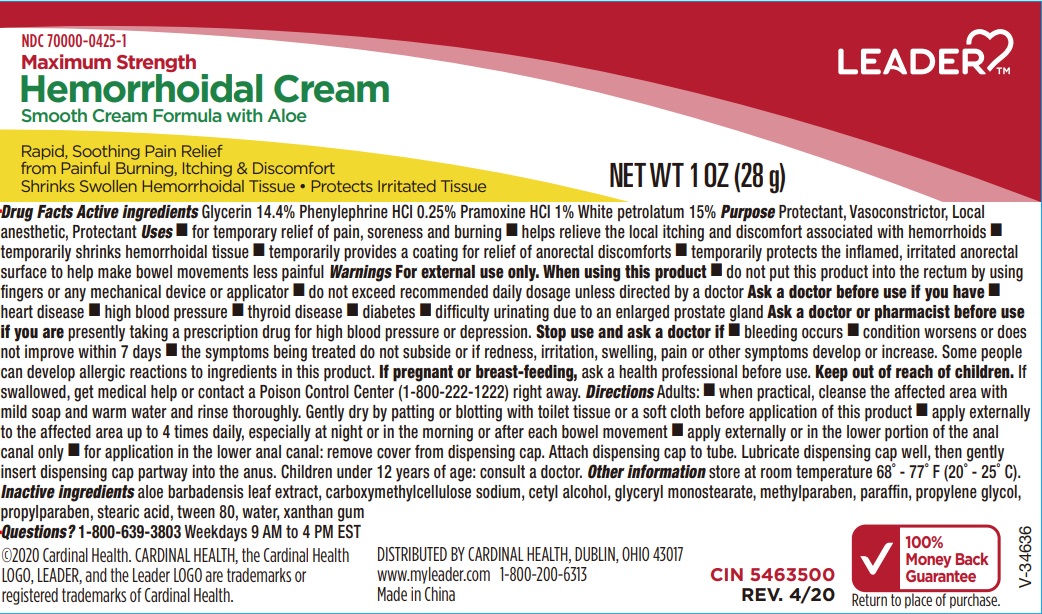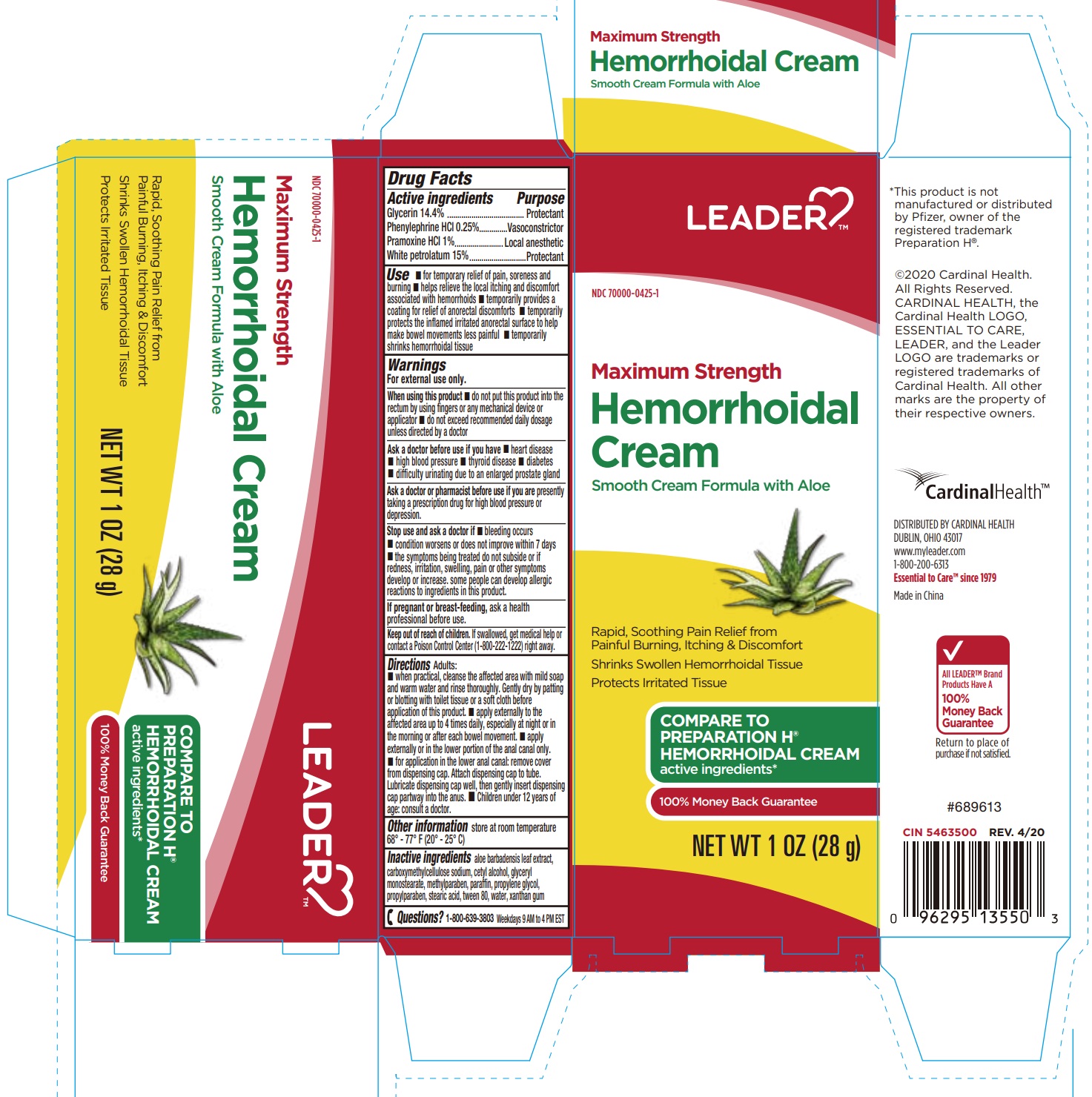 DRUG LABEL: Hemorrhoidal Cream
NDC: 70000-0425 | Form: CREAM
Manufacturer: Cardinal Health 110, LLC. dba Leader
Category: otc | Type: HUMAN OTC DRUG LABEL
Date: 20231025

ACTIVE INGREDIENTS: PRAMOXINE HYDROCHLORIDE 0.28 g/28 g; GLYCERIN 4.032 g/28 g; PHENYLEPHRINE HYDROCHLORIDE 0.07 g/28 g; PETROLATUM 4.2 g/28 g
INACTIVE INGREDIENTS: PROPYLENE GLYCOL; PROPYLPARABEN; GLYCERYL MONOSTEARATE; STEARIC ACID; METHYLPARABEN; POLYSORBATE 80; XANTHAN GUM; WATER; CARBOXYMETHYLCELLULOSE SODIUM; ALOE VERA LEAF; CETYL ALCOHOL; PARAFFIN

MAX STRENTH PAIN RELIEF HEMORRHOIDAL CREAM

Active ingredients

Glycerin 14.4%

Phenylephrine HCl 0.25%

Pramoxine HCl 1%

White petrolatum 15%

Purpose

Protectant

Vasoconstrictor

Local anesthetic

Protectant

Uses

- for temporary relief of pain, soreness and burning
- helps relieve the local itching and discomfort associated with hemorrhoids
- temporarily provides a coating for relief of anorectal discomforts
- temporarily protects the inflamed irritated anorectal surface to help make bowel movements less painful
- temporarily shrinks hemorrhoidal tissue

Warnings

For external use only.

When using this product

- do not put this product into the rectum by using fingers or any mechanical device or applicator
- do not exceed recommended daily dosage unless directed by a doctor

Ask a doctor before use if you have

- heart disease
- high blood pressure
- thyroid disease
- diabetes
- difficulty urinating due to an enlarged prostate gland

Ask a doctor or pharmacist before use if you are

presently taking a prescription drug for high blood pressure or depression.

Stop use and ask a doctor if

- bleeding occurs
- condition worsens or does not improve within 7 days
- the symptoms being treated do not subside or if redness, irritation, swelling, pain or other symptoms develop or increase. Some people can develop allergic reactions to ingredients in this product.

If pregnant or breast-feeding,

ask a health professional before use.

Keep out of reach of children.

If swallowed, get medical help or contact a Poison Control Center (1-800-222-1222) right away.

Directions

Adults:

Children under 12 years of age: consult a doctor.

- when practical, cleanse the affected area with mild soap and warm water and rinse thoroughly. Gently dry by patting or blotting with toilet tissue or a soft cloth before application of this product.
- apply externally to the affected area up to 4 times daily, especially at night or in the morning or after each bowel movement.
- apply externally or in the lower portion of the anal canal only.
- for application in the lower anal canal: remove cover from dispensing cap. Attach dispensing cap to tube. Lubricate dispensing cap well, then gently insert dispensing cap partway into the anus.

Other Information

store at room temperature 68° - 77° F (20° - 25° C).

Inactive ingredients

aloe barbadensis leaf extract, carboxymethylcellulose sodium, cetyl alcohol, glyceryl monostearate, methylparaben, paraffin, propylene glycol, propylparaben, stearic acid, tween 80, water, xanthan gum

Questions?

1-800-639-3803 Weekdays 9 AM to 4 PM EST

Section Type change

The section type INSTRUCTIONS FOR USE SECTION has been updated to DOSAGE & ADMINISTRATION SECTION. The information within the section stays the same.